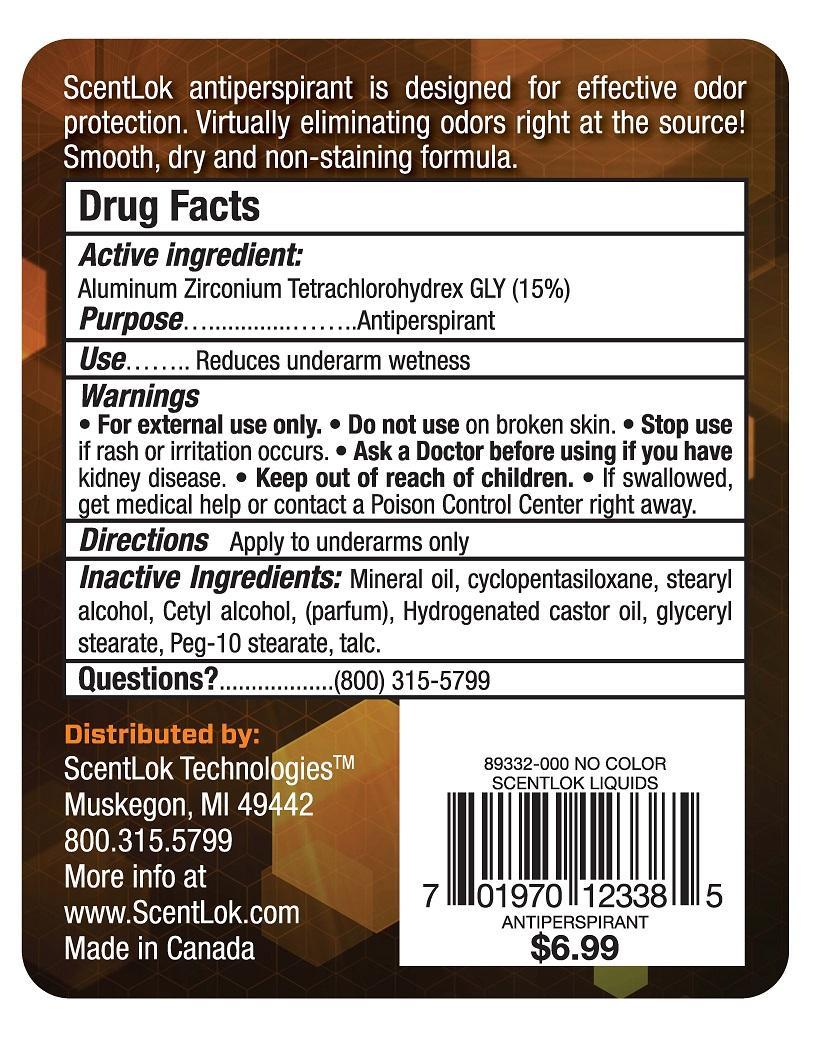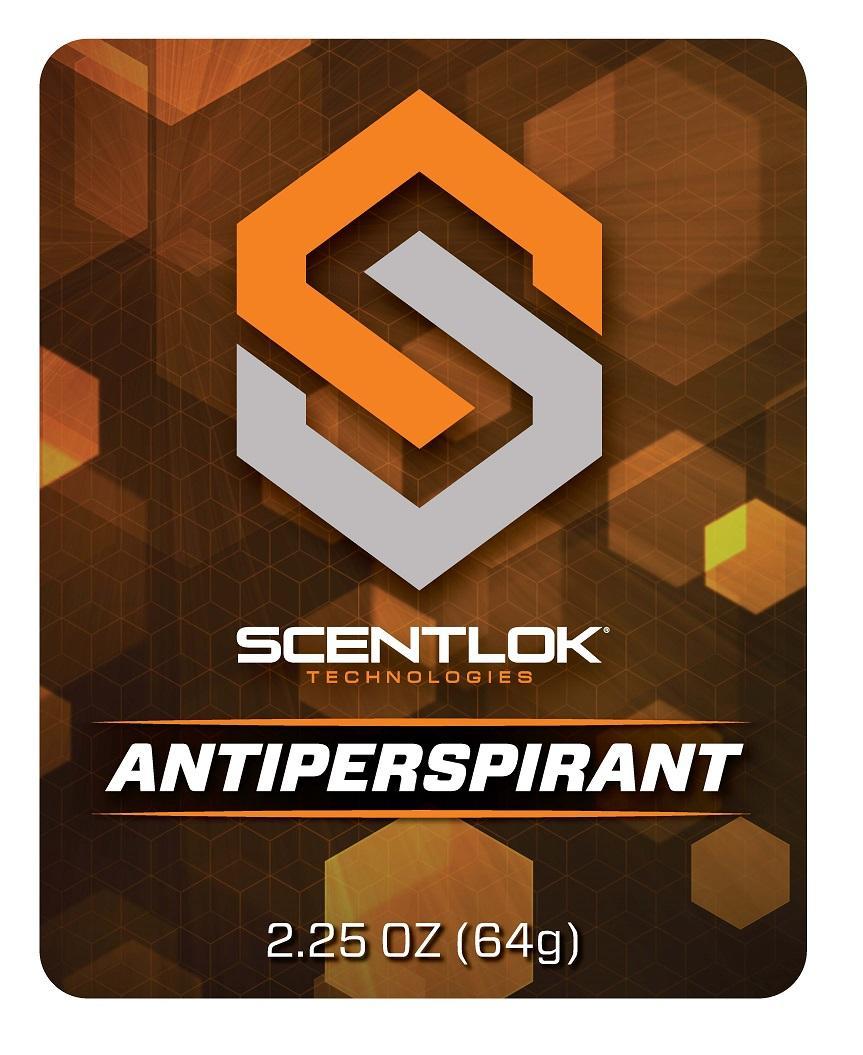 DRUG LABEL: SCENTLOK TECHNOLOGIES ANTIPERSPIRANT
NDC: 69757-101 | Form: GEL
Manufacturer: ALS ENTERPRISES INC
Category: otc | Type: HUMAN OTC DRUG LABEL
Date: 20150502

ACTIVE INGREDIENTS: ALUMINUM ZIRCONIUM TETRACHLOROHYDREX GLY 15 g/100 g
INACTIVE INGREDIENTS: MINERAL OIL; CYCLOMETHICONE 5; STEARYL ALCOHOL; CETYL ALCOHOL; HYDROGENATED CASTOR OIL; GLYCERYL MONOSTEARATE; PEG-10 STEARATE; TALC

ACTIVE INGREDIENT

ALUMINUM ZIRCONIUM TETRACHLOROHYDREX GLY (15%)

PURPOSE

ANTIPERSPIRANT

USE

REDUCES UNDERARM WETNESS

WARNINGS

- FOR EXTERNAL USE ONLY.
- DO NOT USE ON BROKEN SKIN.
- STOP USE IF RASH DEVELOPS.
- ASK A DOCTOR BEFORE USING IF YOU HAVE KIDNEY DISEASE.

- KEEP OUT OF REACH OF CHILDREN.
- IF SWALLOWED, GET MEDICAL HELP OR CONTACT A POISON CONTROL CENTER RIGHT AWAY.

DIRECTIONS

APPLY TO UNDERARMS ONLY.

INACTIVE INGREDIENTS

MINERAL OIL, CYCLOPENTASILOXANE, STEARYL ALCOHOL, CETYL ALCOHOL, FRAGRANCE/PARFUM, HYDROGENATED CASTOR OIL, GLYCERYL STEARATE, PEG-10 STEARATE, TALC.

QUESTIONS?

(800) 315-5799